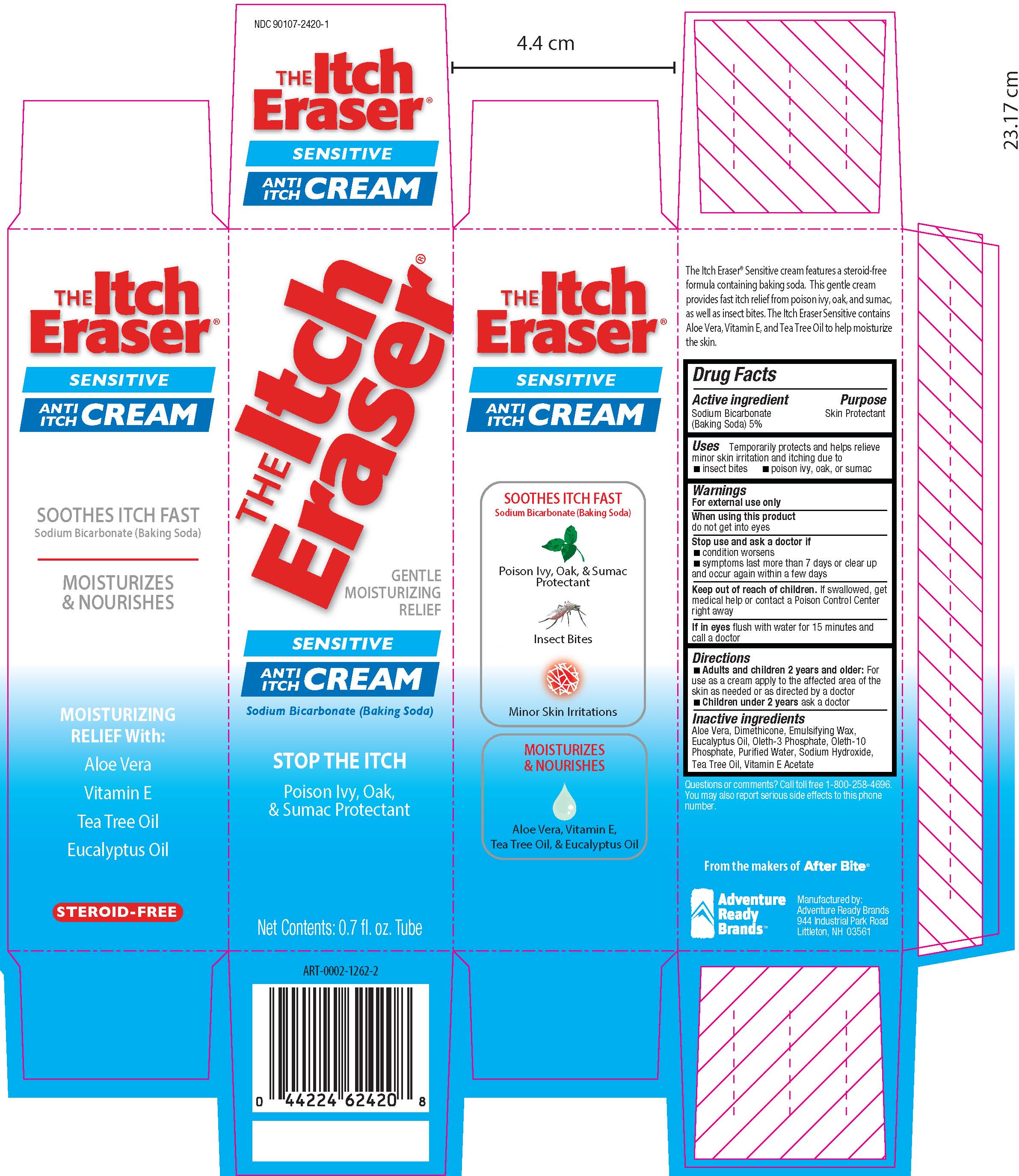 DRUG LABEL: The Itch Eraser Sensitive
NDC: 90107-2420 | Form: CREAM
Manufacturer: Adventure Ready Brands
Category: otc | Type: HUMAN OTC DRUG LABEL
Date: 20200901

ACTIVE INGREDIENTS: SODIUM BICARBONATE 50 mg/1 g
INACTIVE INGREDIENTS: ALOE VERA LEAF; DIMETHICONE; EUCALYPTUS OIL; OLETH-3 PHOSPHATE; OLETH-10; PHOSPHATE ION; WATER; SODIUM HYDROXIDE; .ALPHA.-TOCOPHEROL ACETATE; TEA TREE OIL

The Itch Eraser Sensitive Cream

Active Ingredient

Sodium Bicarbonate (BakingSoda) 5%

Purpose

Skin Protectant

Uses

Temporarily protects and helps relieve minor skin irritation and itching due to:

- insect bites
- poison: ivy, oak, and sumac

Warnings

For external use only

When using this product

- do not get into eyes

Stop use and ask a doctor if

- condition worsens
- symptoms last more than 7 days or clear up and occur again within a few days

Keep out of reach of children.

If swallowed, get medical help or contact a Poison Control Center right away.

If in eyes flush with water for 15 minutes and call a doctor

Directions

- Adults and children 2 years and older dab directly on bite or sting, rub gently and re-apply as needed
- children under 2 years of age: ask a doctor.

Inactive Ingredients

Aloe Vera, Dimethicone, Emulsifying Wax, Eucalyptus Oil, Oleth-3 Phosphate, Oleth-10, Phosphate, Purified Water, Sodium Hydroxide, Vitamin E Acetate, and Tea Tree Oil